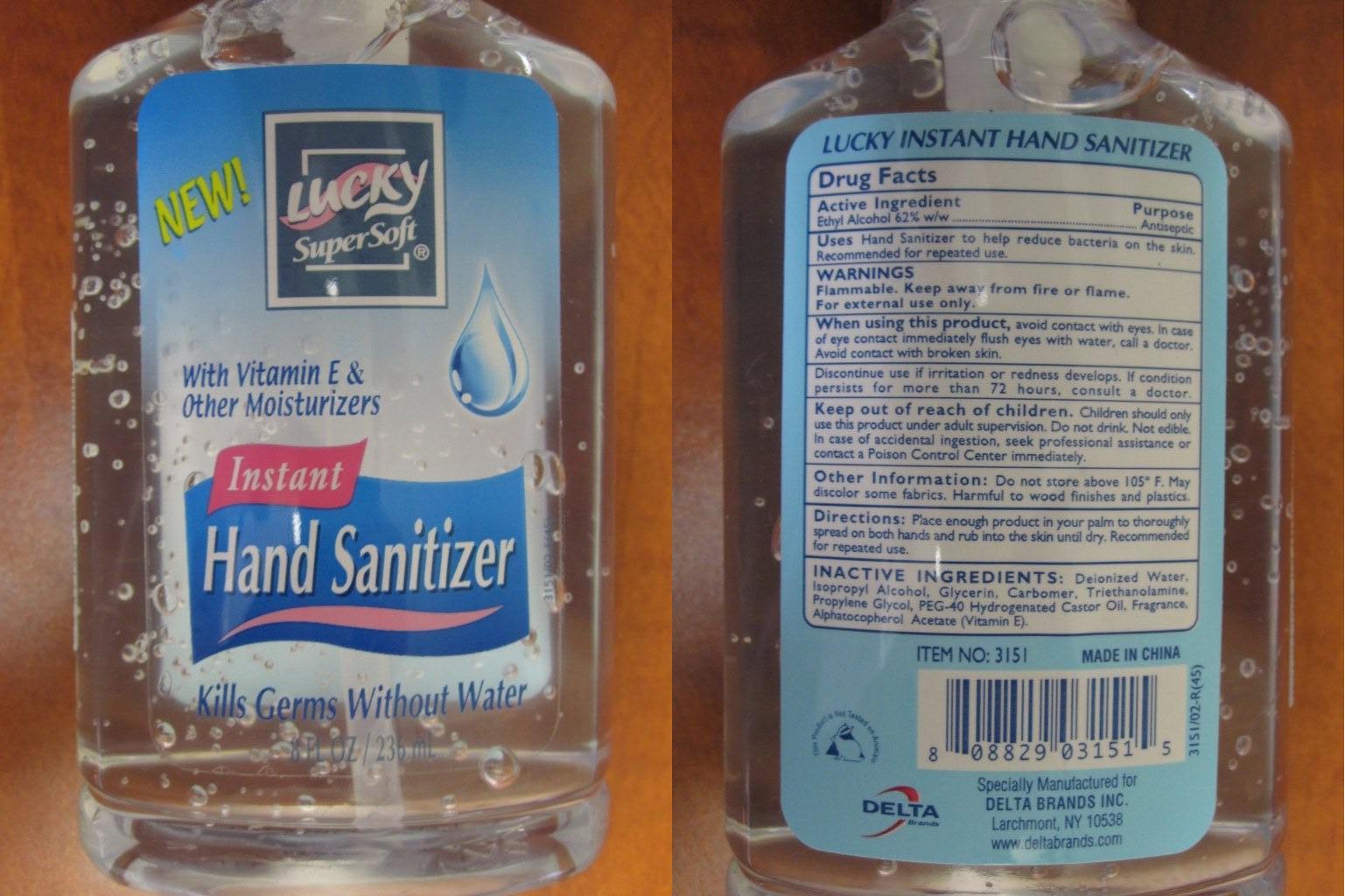 DRUG LABEL: Lucky Instant Hand Sanitizer with Vitamin E and Moisturizers
NDC: 20276-150 | Form: LIQUID
Manufacturer: Delta Brands Inc
Category: otc | Type: HUMAN OTC DRUG LABEL
Date: 20230629

ACTIVE INGREDIENTS: ALCOHOL 62 mL/100 mL
INACTIVE INGREDIENTS: WATER; ISOPROPYL ALCOHOL; GLYCERIN; TROLAMINE; PROPYLENE GLYCOL; POLYOXYL 40 HYDROGENATED CASTOR OIL; ALPHA-TOCOPHEROL ACETATE

LuckyHndSntzrwthMstrzrs&VitEAlch62

Active Ingredient

Ethyl Alcohol 62%

Purpose

Antiseptic

Uses

Hand sanitizer to help reduce bacteria on the skin. Recommended for repeated use.

Warnings

Flammable. Keep away from fire and flame. For external use only

When using this product

avoid contact with eyes and mucous membranes. In case of eye contact; immediately flush eyes with water, call a doctor. Avoid contact with broken skin.

Discontinue use if irritation develops. If condition persists for more than 72 hours, consult a doctor.

Keep out of reach of children

Children can only use this product with adult supervision. Do not drink. Not edible. In case of accidental ingestion seek professional assistance or Poison Control Center immediately.

Other Information

Do not store above 105F. May discolor some fabrics. Harmful to wood finishes and plastics.

Directions

Place enough product in your palm to thoroughly spread on both hands and rub into the skin until dry. Recommended for repeated use.

Inactive ingredients

Deionized Water, Isopropyl Alcohol, Glycerin, Carbomer, Triethanolamine, Propylene Glycol, PEG-40 Hydrogenated Castor Oil, Fragrance, Alphatocopherol Acetate (Vitamin E)